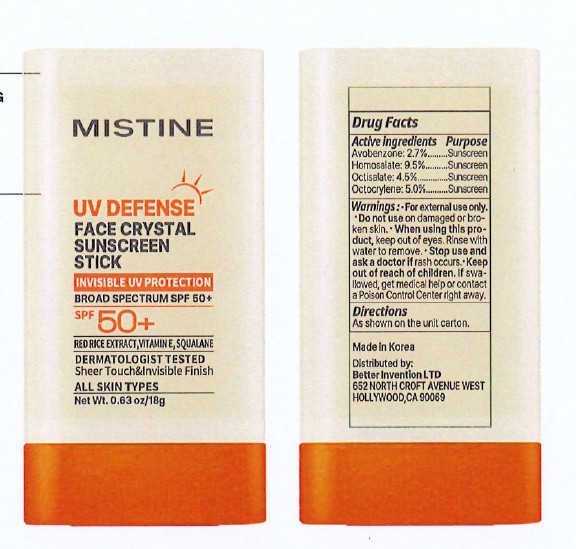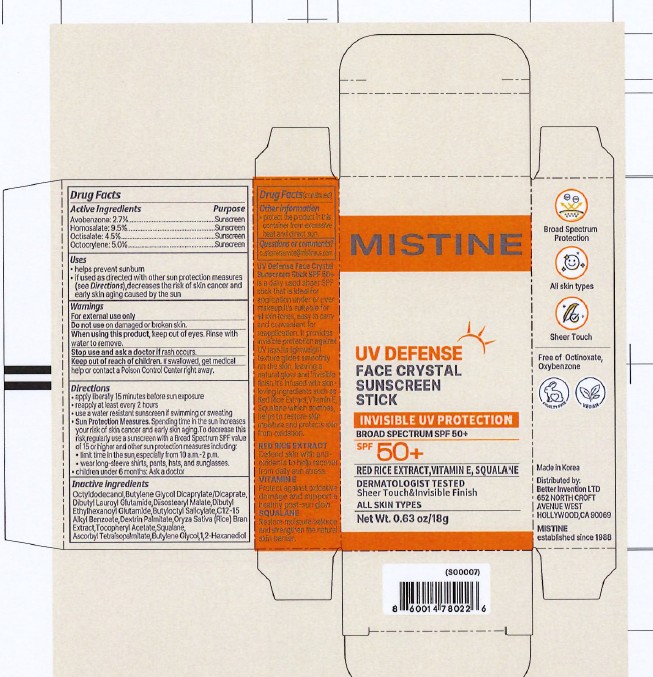 DRUG LABEL: MISTINE UV DEFENSE FACE SUNSCREEN SPF50
NDC: 87458-005 | Form: CREAM
Manufacturer: BETTER INVENTION LTD
Category: otc | Type: HUMAN OTC DRUG LABEL
Date: 20260226

ACTIVE INGREDIENTS: OCTISALATE 4.5 g/100 mg; AVOBENZONE 2.7 g/100 mg; OCTOCRYLENE 5 g/100 mg; HOMOSALATE 9.5 g/100 mg
INACTIVE INGREDIENTS: OCTYLDODECANOL; BUTYLOCTYL SALICYLATE; DIBUTYL LAUROYL GLUTAMIDE; BUTYLENE GLYCOL; SQUALANE; DIISOSTEARYL MALATE; ORYZA SATIVA (RICE) BRAN; .ALPHA.-TOCOPHEROL ACETATE, DL-; ASCORBYL TETRAISOPALMITATE; 1,2-HEXANEDIOL; DIBUTYL ETHYLHEXANOYL GLUTAMIDE; DEXTRIN PALMITATE (CORN; 20000 MW); BUTYLENE GLYCOL DICAPRYLATE/DICAPRATE; C12-15 ALKYL BENZOATE

MISTINE UV DEFENSE FACE CRYSTAL SUNSCREEN STICK SPF 50+

Active ingredients

Avobenzone: 2.7%
Homosalate: 9.5%
Octisalate:4.5%
Octocrylene: 5%

Purpose

Sunscreen

USES

- helps prevent sunburn
- if used as directed with other sun protection measures (see Directions), decreases the risk of skin cancer and early skin aging caused by the sun.

Warnings

For external use only

Do not use on damaged or broken skin.

When using this product, keep out of eyes. Rinse with water to remove.

Stop use and ask a doctor if rash occurs.

Keep out of reach of children. If swallowed, get medical help or contact a Poison Control Center right away.

DIRECTIONS

- apply liberally 15 minutes before sun exposure
- reapply at least every 2 hours
- use a water resistant sunscreen if swimming or sweating
- Sun Protection Measures. Spending time in the sun increases your risk of skin cancer and early skin aging. To decrease this risk regularly use a sunscreen with a Broad Spectrum SPF value of 15 or higher and other sun protection measures including:
- limit time in the sun especially from 10 a.m. - 2 p.m.
- wear long-sleeve shirts, pants, hats, and sunglasses.
- children under 6 months: Ask a doctor

Inactive ingredients

Octyldodecanol, Butylene Glycol Dicaprylate/Dicaprate, Dibutyl Lauroyl Glutamide, Diisostearyl Malate, Dibutyl Ethylhexanoyl Glutamide, Butyloctyl Salicylate, C12-15 Alkyl Benzoate, Dextrin Palmitate, Tocopheryl Acetate, Squalane, Ascorbyl Tetraisopalmitate, Butylene Glycol, Oryza Sativa (Rice) Bran Extract, 1,2-Hexanediol.

OTHER INFORMATION

- protect the product in this container from excessive heat and direct sun.